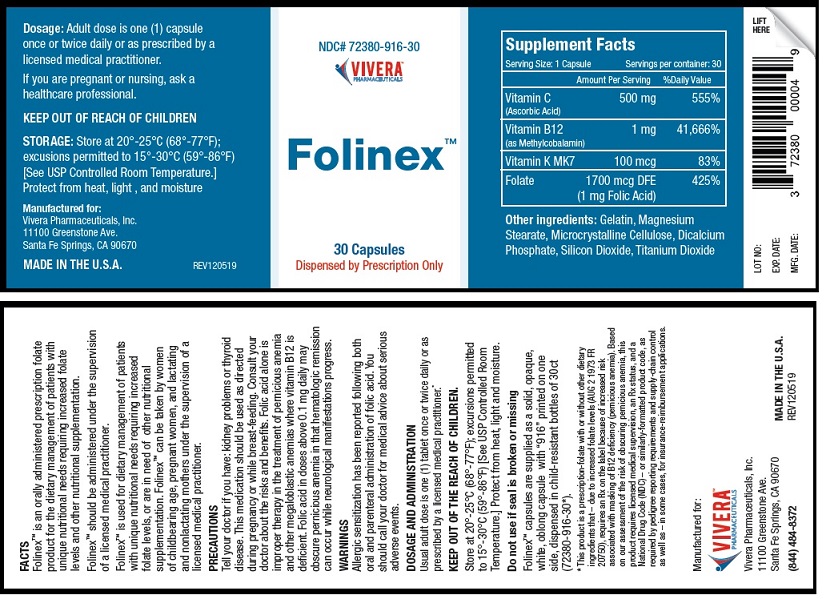 DRUG LABEL: Folinex
NDC: 72380-916 | Form: CAPSULE
Manufacturer: Vivera Pharmaceuticals, Inc.
Category: prescription | Type: HUMAN PRESCRIPTION DRUG LABEL
Date: 20200210

ACTIVE INGREDIENTS: ASCORBIC ACID 355 mg/1 1; METHYLCOBALAMIN 1 mg/1 1; VITAMIN K7 100 ug/1 1; FOLIC ACID 1 mg/1 1
INACTIVE INGREDIENTS: GELATIN; MAGNESIUM STEARATE; MICROCRYSTALLINE CELLULOSE; ANHYDROUS DIBASIC CALCIUM PHOSPHATE; SILICON DIOXIDE; TITANIUM DIOXIDE

FOLINEXTM

FACTS

Folinex™ is an orally administered prescription folate
product for the dietary management of patients with
unique nutritional needs requiring increased folate
levels and other nutritional supplementation.

Folinex™ should be administered under the supervision
of a licensed medical practitioner.

Folinex™ is used for dietary management of patients
with unique nutritional needs requiring increased
folate levels, or are in need of other nutritional
supplementation. Folinex™ can be taken by women
of childbearing age, pregnant women, and lactating
and nonlactating mothers under the supervision of a
licensed medical practitioner.

PRECAUTIONS

Tell your doctor if you have: kidney problems or thyroid
disease. This medication should be used as directed
during pregnancy or while breast-feeding. Consult
your doctor about the risks and benefits. Folic acid alone is
improper therapy in the treatment of pernicious anemia
and other megaloblastic anemias where vitamin B12 is
deficient. Folic acid in doses above 0.1 mg daily may
obscure pernicious anemia in that hematologic remission
can occur while neurological manifestations progress.

WARNINGS

Allergic sensitization has been reported following both
oral and parenteral administration of folic acid. You
should call your doctor for medical advice about serious
adverse events.

DOSAGE AND ADMINISTRATION

Usual adult dose is one (1) tablet once or twice daily or as
prescribed by a licensed medical practitioner.*

PREGNANCY

If you are pregnant or nursing, ask a
healthcare professional.

OTHER SAFETY INFORMATION

KEEP OUT OF THE REACH OF CHILDREN.

Store at 20°-25°C (68°-77°F); excursions permitted
to 15°-30°C (59°-86°F) [See USP Controlled Room
Temperature.] Protect from heat, light and moisture.

Do not use if seal is broken or missing.

Folinex™ capsules are supplied as a solid, opaque,
white, oblong capsule with “916” printed on one
side, dispensed in child-resistant bottles of 30ct
(72380-916-30*).

OTHER SAFETY INFORMATION

* This product is a prescription-folate with or without other dietary
ingredients that – due to increased folate levels (AUG 2 1973 FR
20750), requires an Rx on the label because of increased risk
associated with masking of B12 deficiency (pernicious anemia). Based
on our assessment of the risk of obscuring pernicious anemia, this
product requires licensed medical supervision, an Rx status, and a
National Drug Code (NDC) – or similarly-formatted product code, as
required by pedigree reporting requirements and supply-chain control
as well as – in some cases, for insurance-reimbursement applications.

Package Label

NDC# 72380-916-30

VIVERA™
PHARMACEUTICALS

Folinex™

30 Capsules

Dispensed by Prescription Only

Supplement Facts
Serving Size: 1 Capsule Servings per container: 30
Amount Per Serving %Daily Value
Vitamin C 500 mg 555%
(Ascorbic Acid)
Vitamin B12 1 mg 41,666%
(as Methylcobalamin)
Vitamin K MK7 100 mcg 83%
Folate 1700 mcg DFE 425%
(1 mg Folic Acid)

Other ingredients: Gelatin, Magnesium
Stearate, Microcrystalline Cellulose, Dicalcium
Phosphate, Silicon Dioxide, Titanium Dioxide

Dosage: Adult dose is one (1) capsule
once or twice daily or as prescribed by a
licensed medical practitioner.

If you are pregnant or nursing, ask a
healthcare professional.

KEEP OUT OF REACH OF CHILDREN

STORAGE: Store at 20°-25°C (68°-77°F);
excusions permitted to 15°-30°C (59°-86°F)
[See USP Controlled Room Temperature.]
Protect from heat, light , and moisture

Manufactured for:
Vivera Pharmaceuticals, Inc.
11100 Greenstone Ave.
Santa Fe Springs, CA 90670

MADE IN THE U.S.A. REV120519

LOT NO:
EXP. DATE:
MFG. DATE:

3 72389 00004 9

RES